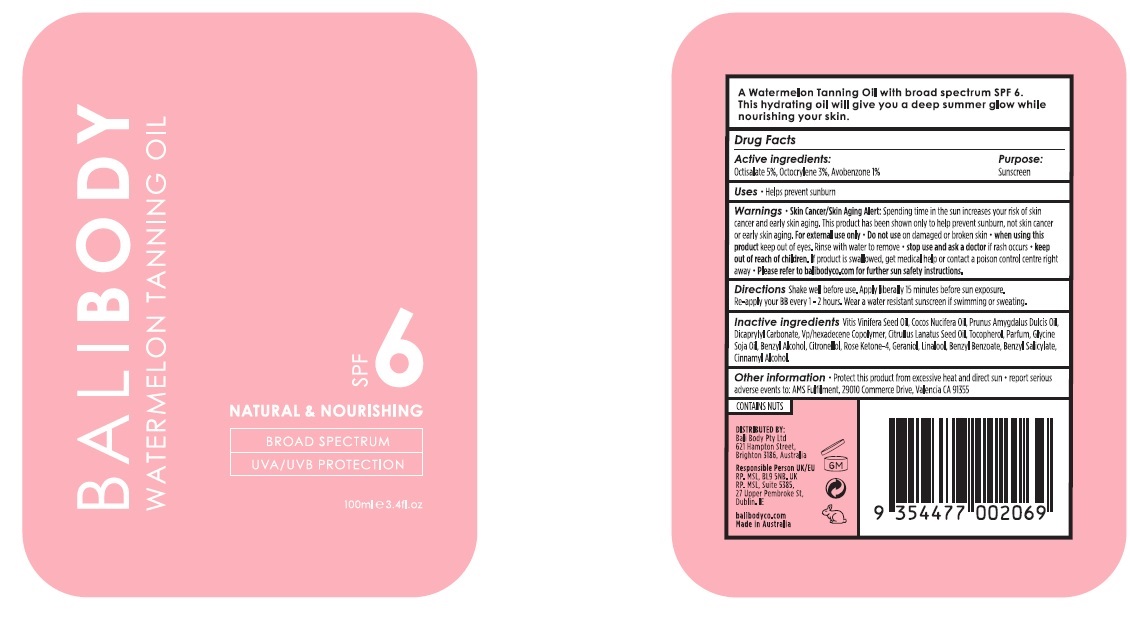 DRUG LABEL: Bali Body Watermelon Tanning Oil SPF 6
NDC: 70630-0033 | Form: OIL
Manufacturer: Bali Body Pty Ltd
Category: otc | Type: HUMAN OTC DRUG LABEL
Date: 20241021

ACTIVE INGREDIENTS: OCTOCRYLENE 30 mg/1 mL; OCTISALATE 50 mg/1 mL; AVOBENZONE 10 mg/1 mL
INACTIVE INGREDIENTS: CINNAMYL ALCOHOL; LINALOOL, (+/-)-; BENZYL BENZOATE; DICAPRYLYL CARBONATE; GRAPE SEED OIL; ALMOND OIL; COCONUT OIL; WATERMELON SEED OIL; SOYBEAN OIL; TOCOPHEROL; BENZYL ALCOHOL; VINYLPYRROLIDONE/HEXADECENE COPOLYMER; GERANIOL; BENZYL SALICYLATE; .BETA.-CITRONELLOL, (+/-)-

Bali Body Watermelon Tanning Oil SPF6

Active ingredients

Octisalate 5%
Octocrylene 3%
Avobenzone 1%

Purpose

Sunscreen

Uses

- Helps prevent sunburn

Warnings

Skin Cancer/Skin Aging Alert: Spending time in the sun increases your risk of skin cancer and early skin aging. This product has been shown only to prevent sunburn, not skin cancer or early skin aging.

For external use only.

Do not use

on damaged or broken skin.

When using this product

keep out of eyes. Rinse with water to remove.

Stop use and ask a doctor

if rash occurs.

Keep out of reach of children.

If product is swallowed, get medical help or contact a poison control centre right away. Please refer to balibody.com for further sun safety instructions.

Directions

Shake well before use. Apply liberally 15 minutes before sun exposure. Re-apply your BB every 1-2 hours. Wear a water resistant sunscreen if swimming or sweating.

Inactive ingredients:

Vitis Vinifera Seed Oil, Cocos Nucifera Oil, Prunus Amygdalus Dulcis Oil, Dicaprylyl Carbonate, Vp/hexadecene Copolymer, Citrullus Lanatus Seed Oil, Tocopherol, Parfum, Glycine Soja Oil, Benzyl Alcohol, Citronellol, Rose Ketone-4, Geraniol, Linalool, Benzyl Benzoate, Benzyl Salicylate, Cinnamyl Alcohol.

Other information

- Protect this product from excessive heat and direct sun
- Report serious adverse events to: AMS Fulfilment, 29010 Commerce Drive, Valencia CA 91355